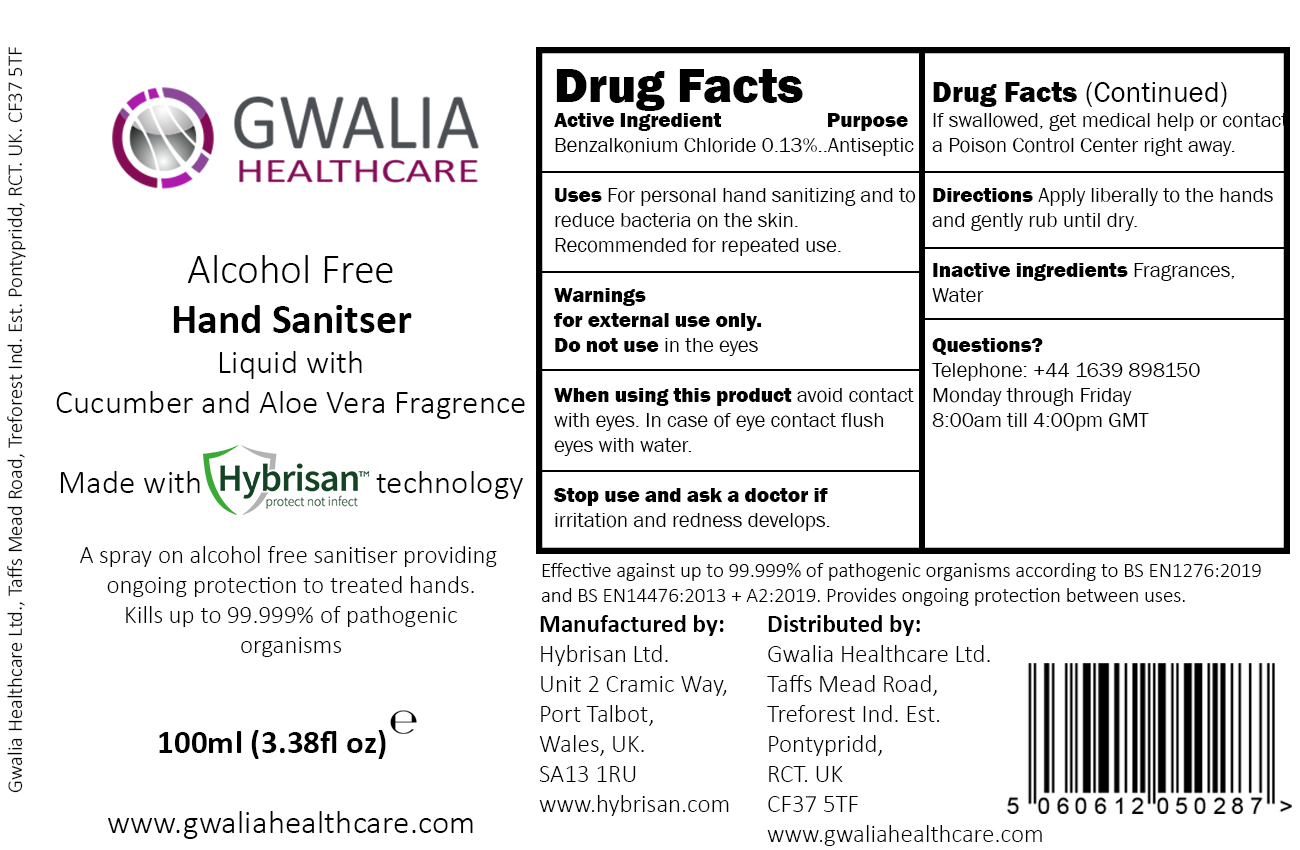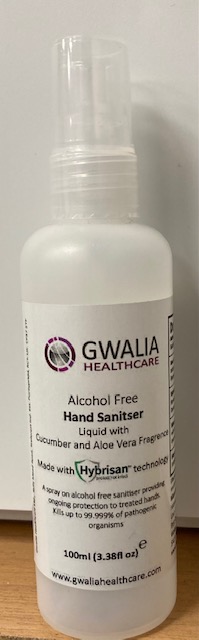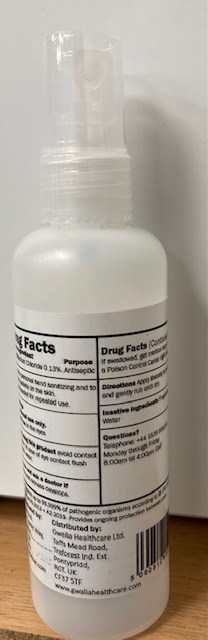 DRUG LABEL: Alcohol Free Hand Sanitizer
NDC: 81685-321 | Form: SOLUTION
Manufacturer: Hybrisan Ltd
Category: otc | Type: HUMAN OTC DRUG LABEL
Date: 20210307

ACTIVE INGREDIENTS: BENZALKONIUM CHLORIDE 0.13 g/100 mL
INACTIVE INGREDIENTS: PHENYLETHYL ALCOHOL; 3A,4,5,6,7,7A-HEXAHYDRO-1H-4,7-METHANOINDEN-6-YL ACETATE; ISOMETHYL-.ALPHA.-IONONE; LIMONENE, (+)-; .ALPHA.-HEXYLCINNAMALDEHYDE; .ALPHA.-TERPINEOL; LINALOOL, (+/-)-; METHYL HEPTINE CARBONATE

Hybrisan Alcohol Free Aloe Vera & Cuccumber Hand Sanitizer

Drug Facts

Benzalkonium Chloride 0.13% Purpose Antiseptic

Drug Facts

Antiseptic

Drug Facts

For personal hand sanitizing and to reduce bacteria on the skin. Recommended for repeated use

Avoid contact with eyes. In the case of eye contact flush eyes with water.

Warnings

When using this product avoid contact with eyes. In case of eye contact flush eyes with water.

Ask Doctor

Stop use and ask a doctor if irritation and redness develop

Inactive ingredients

Fragrances, water

Directions

Apply liberally to the hands and gently rub until dry

Questions?

Telephone: 44-1639-898150 Monday through Friday 8:00am til 4:30pm UK time

Keep out of reach of children. If swallowed, get medical help or contact a Poison Control Center right away.

Package quantity

100ml (3.38 Floz) NDC 81685-321-10